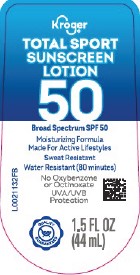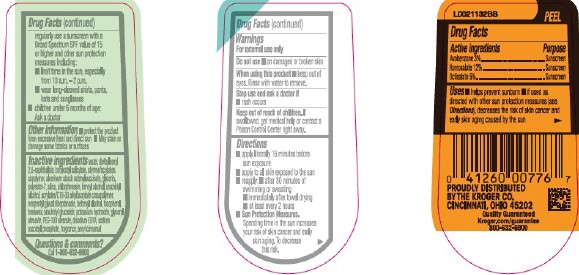 DRUG LABEL: Sport Sunscreen SPF 50
NDC: 59450-940 | Form: LOTION
Manufacturer: The Kroger Co.
Category: otc | Type: HUMAN OTC DRUG LABEL
Date: 20260227

ACTIVE INGREDIENTS: AVOBENZONE 30 mg/1 mL; HOMOSALATE 120 mg/1 mL; OCTISALATE 50 mg/1 mL
INACTIVE INGREDIENTS: WATER; DIETHYLHEXYL 2,6-NAPHTHALATE; BUTYLOCTYL SALICYLATE; STYRENE/ACRYLAMIDE COPOLYMER (500000 MW); ALUMINUM STARCH OCTENYLSUCCINATE; GLYCERIN; POLYESTER-7; SILICON DIOXIDE; CHLORPHENESIN; BENZYL ALCOHOL; ARACHIDYL ALCOHOL; CARBOMER COPOLYMER TYPE B (ALLYL PENTAERYTHRITOL CROSSLINKED); NEOPENTYL GLYCOL DIHEPTANOATE; DOCOSANOL; TOCOPHEROL; YELLOW WAX; ARACHIDYL GLUCOSIDE; POTASSIUM HYDROXIDE; GLYCERYL MONOSTEARATE; PEG-100 STEARATE; EDETATE DISODIUM ANHYDROUS; SODIUM ASCORBYL PHOSPHATE; .ALPHA.-AMYLCINNAMALDEHYDE

Kroger D40.000/D40AA
Sport Sunscreen Lotion SPF 50

Active ingredients

Avobenzone 3%

Homosalate 12%

Octisalate 5%

Purpose

Sunscreen

Uses

- helps prevent sunburn
- if used as directed with other sun protections measures (see Directions), decreases the risk of skin cancer and early skin aging caused by the sun

Warnings

For external use only

Do not use

- on damaged or broken skin

When using this product

- keep out of eyes. Rinse with water to remove.

Stop use and ask a doctor if

- rash occurs

Keep out of reach of children.

If swallowed, get medical help or contact a Poison Control Center right away.

Directions

- apply liberally 15 minutes before sun exposure
- apply to all skin exposed to the sun
- reapply:
- after 80 minutes of swimming or sweating
- immediately after towel drying
- at least every 2 hours
- Sun Protection Measures. Spending time in the sun increases your risk of skin cancer and early skin aging. To decrease this risk, regularly use a sunscreen with a Broad Spectrum SPF value of 15 or higher and other sun protection measures including:
- limit time in the sun, especially from 10 a.m.–2 p.m.
- wear long-sleeved shirts, pants, hats and sunglasses
- children under 6 months of age: Ask a doctor

Other information

- Protect the product from excessive heat and direct sun
- May stain or change some fabrics or surfaces

Inactive ingredients

water, diethylhexyl 2,6-naphthalate, butyloctyl salicylate, styrene/acrylates copolymer, aluminum starch octenylsuccinate, glycerin, polyester-7, silica, chlorphenesin, benzyl alcohol, arachidyl alcohol, acrylates/C10-30 alkyl acrylate crosspolymer, neopentyl glycol diheptanoate, behenyl alcohol, tocopherol, beeswax, arachidyl glucoside, potassium hydroxide, glyceryl stearate, PEG-100 stearate, disodium EDTA, sodium ascorbyl phosphate, fragrance, amyl cinnamal

Questions & comments?

Call 1-800-632-6900

Adverse Reaction

PROUDLY DISTRIBUTED BY THE KROGER CO. CINCINNATI, OHIO 45202

Quality Guaranteed

Kroger.com/guarantee

800-632-6900

Principal display panel

Kroger®

TOTAL SPORT

SUNSCREEN LOTION 50

Broad Spectrum SPF 50

Moisturizing Formula

Made For Active Lifestyles

Sweat Resistant

Water Resistant (80 minutes)

No Oxybenzone or Octinoxate

UVA/UVB Protection

QUALITY GUARANTEED

1.5 FL OZ (44 mL)